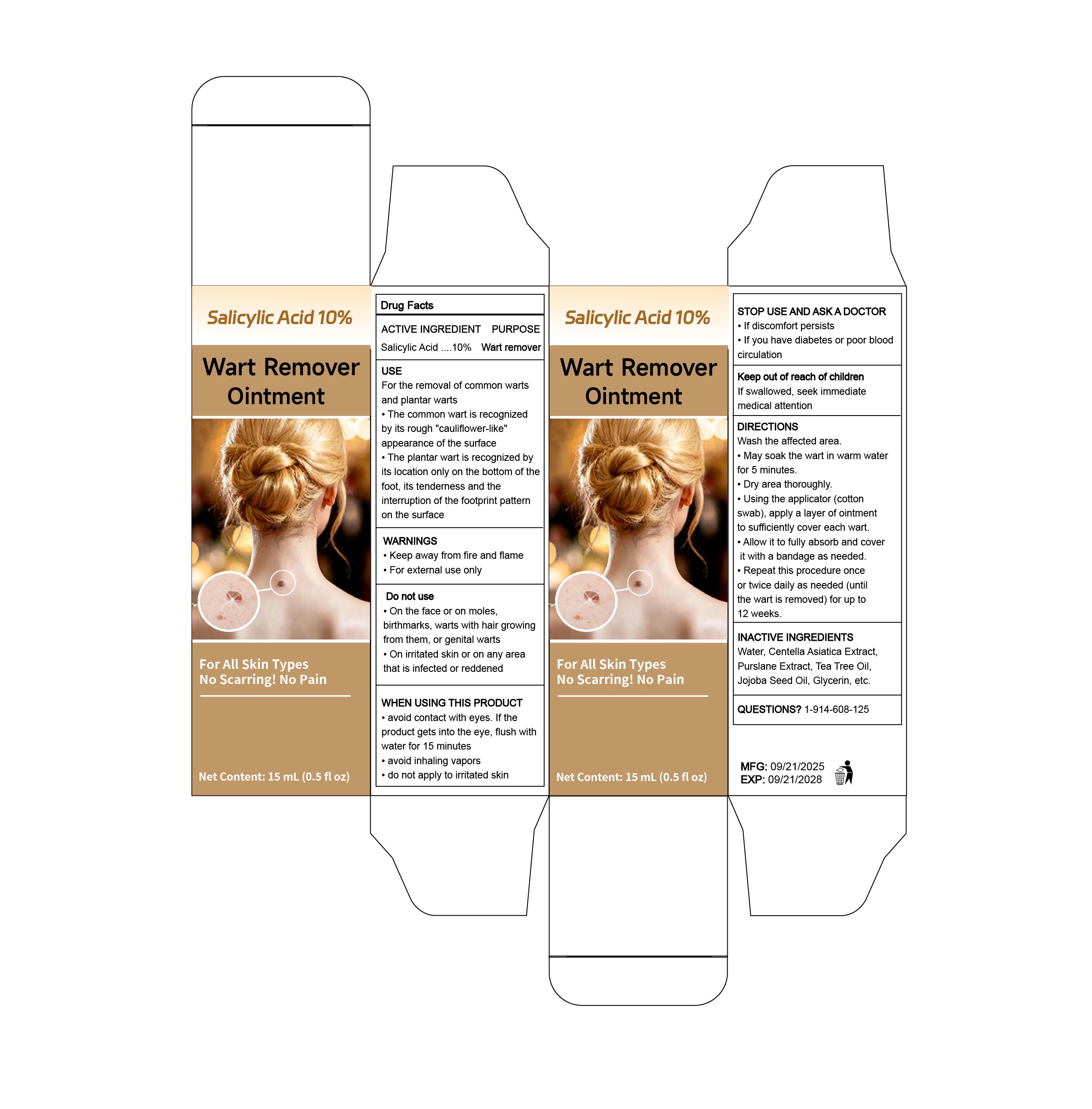 DRUG LABEL: Wart Remover
NDC: 87276-261 | Form: OINTMENT
Manufacturer: Shenzhen Zhenshangzekai Technology Co., Ltd.
Category: otc | Type: HUMAN OTC DRUG LABEL
Date: 20260130

ACTIVE INGREDIENTS: SALICYLIC ACID 10 g/100 g
INACTIVE INGREDIENTS: CENTELLA ASIATICA; JOJOBA OIL; GLYCERIN; WATER; PURSLANE; TEA TREE OIL

ASK DOCTOR

If discomfort persists

If you have diabetes or poor blood circulation

DO NOT USE

on warts with hair growing from them, on moles, birthmarks, or genital warts

on irritated skin or on any area that is infected or reddened

KEEP OUT OF REACH OF CHILDREN

If swallowed,seek immediate medical attention

PURPOSE

wart remover

WHEN USING

avoid contact with eyes. lf the product gets into the eyes, flush with water for 15minutes
avoid inhaling vapors
do not apply to irritated skin

INDICATIONS AND USAGE

Wash the affected area
May soak the wart in warm water for 5 minutes.
Dry area thoroughly.
Using the applicator, coat the wart with a thin layer of ointment to sufficiently covereach wart.
Allow it to fully absorb and cover it with a bandage as needed.Repeat this procedure once or twice daily as needed (until the wart is removed) forup to 12 weeks.

DOSAGE AND ADMINISTRATION

15 ml

WARNINGS

Keep away from fire and flame; For external use only

INACTIVE INGREDIENT

Water, Centella Asiatica Extract, Purslane Extract, Tea Tree Oil, Jojoba Seed Oil, Glycerin

ACTIVE INGREDIENT

salicylic acid 10%